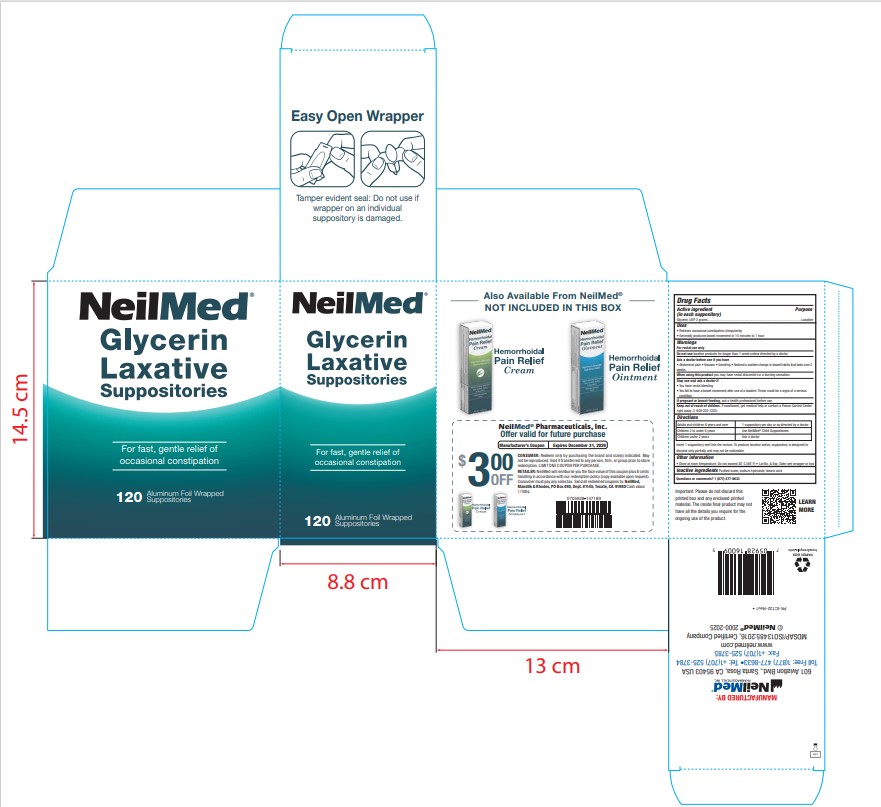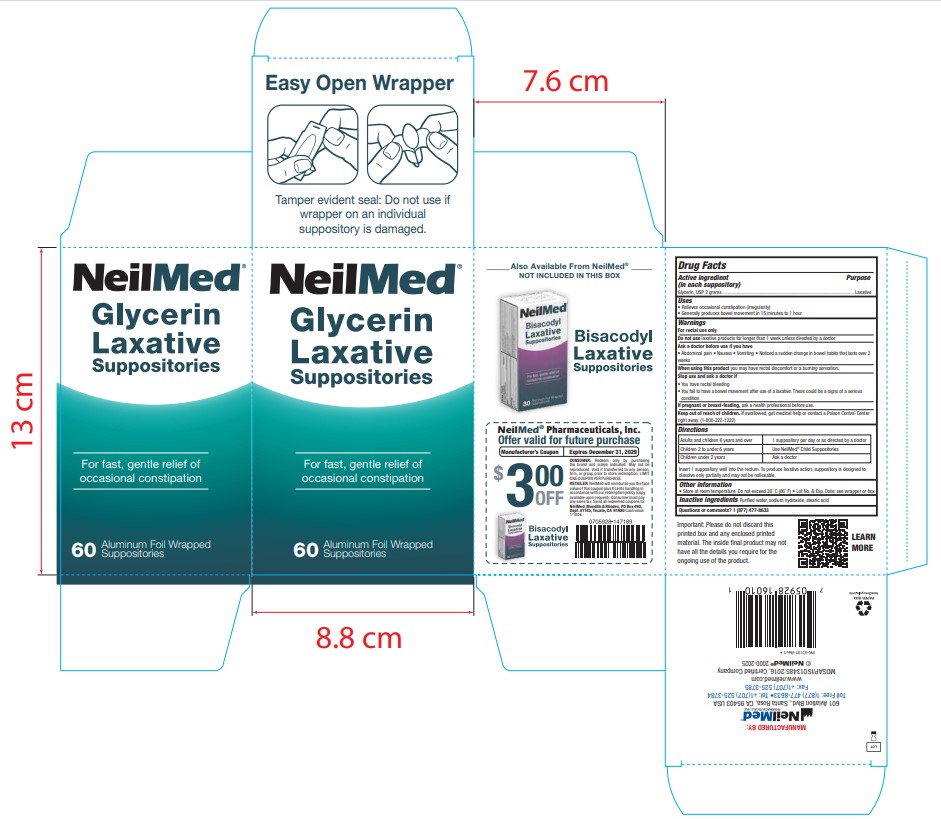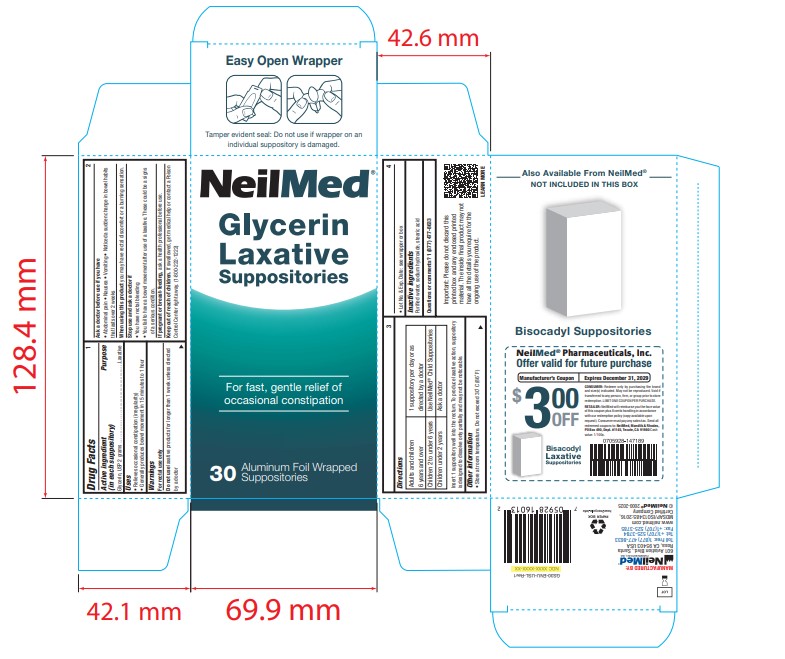 DRUG LABEL: Glycerin Laxative
NDC: 13709-329 | Form: SUPPOSITORY
Manufacturer: Neilmed Pharmaceuticals Inc.
Category: otc | Type: HUMAN OTC DRUG LABEL
Date: 20250620

ACTIVE INGREDIENTS: GLYCERIN 2 g/2.5 g
INACTIVE INGREDIENTS: STEARIC ACID; SODIUM HYDROXIDE; WATER

Glycerin Laxative foil wrapped Suppositories

Drug Facts: Active Ingredient

Active ingredient (in each suppository)
Glycerin, USP 2 grams

Drug Facts

Active ingredient (in each suppository) ...............Purpose
Glycerin, USP 2 grams ...................................... Laxative

Uses

• Relieves occasional constipation (irregularity)
• Generally produces bowel movement in 15 minutes to 1 hour

Warnings

For rectal use only

Do not use

laxative products for longer than 1 week unless directed by a doctor

Ask a doctor before use if you have

• Abdominal pain • Nausea • Vomiting • Noticed a sudden change in bowel habits that lasts over 2 weeks

When using the product

you may have rectal discomfort or a burning sensation.

Stop use and ask a doctor if

- You have rectal bleeding
- You fail to have a bowel movement after use of a laxative. These could be a signs of a serious condition.

If pregnant or breast-feeding,

ask a health professional before use.

Keep out of reach of children.

If swallowed, get medical help or contact a Poison Control Center right away. (1-800-222-1222)

Directions

Adults and children 6 years of age and over | 1 suppository per day or as directed by a doctor.
Children 2 to under 6 years | Use Neilmed Child Suppositories
Children under 2 years | Ask a doctor

Insert 1 suppository well into the rectum. To produce laxative action, suppository is designed to dissolve only partially and may not be noticeable.

Other Information

- Store at room temperature. Do not exceed 30˚ C (86˚ F)
- Lot No. & Exp. Date: see wrapper or box

Inactive ingredients

Purified water, sodium hydroxide, stearic acid

Questions?

Questions or comments? 1 (877) 477-8633

Important:

Please do not discard this printed box and any enclosed printed material. The inside final product may not have all the details you require for the ongoing use of the product.